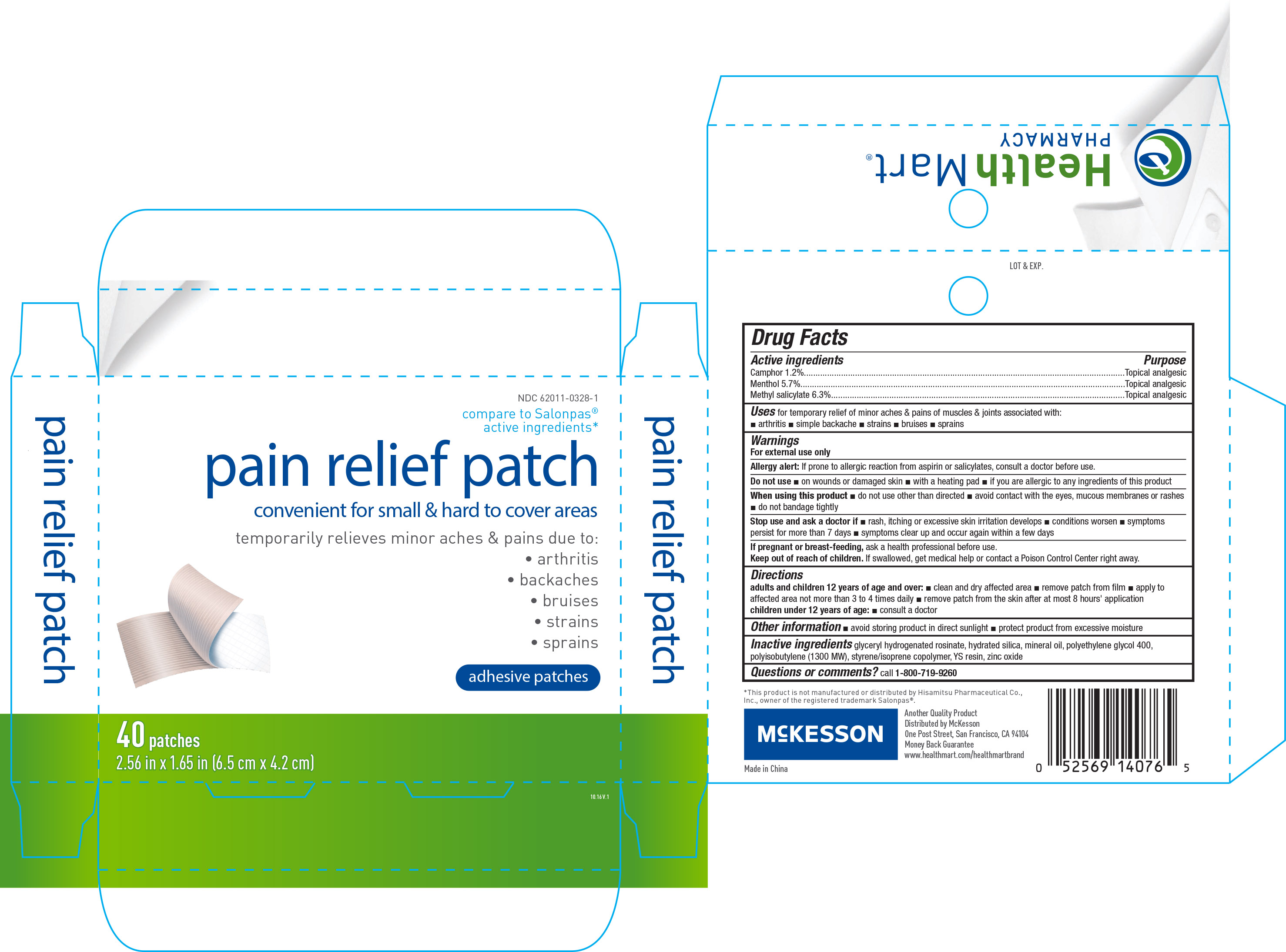 DRUG LABEL: Health Mart Pain Relief
NDC: 62011-0328 | Form: PATCH
Manufacturer: McKesson
Category: otc | Type: HUMAN OTC DRUG LABEL
Date: 20170123

ACTIVE INGREDIENTS: CAMPHOR (SYNTHETIC) 7.1 mg/1 1; MENTHOL 33 mg/1 1; METHYL SALICYLATE 36 mg/1 1
INACTIVE INGREDIENTS: HYDRATED SILICA; MINERAL OIL; POLYETHYLENE GLYCOL 400; POLYISOBUTYLENE (1300 MW); STYRENE; ISOPRENE; ZINC OXIDE

Active ingredients Purpose

Camphor 1.2%.........................................................Topical analgesic

Menthol 5.7%...........................................................Topical analgesic

Methyl salicylate 6.3%...............................................Topical analgesic

Uses

for temporary relief of minor aches & pains of muscles & joints associated with:

- arthritis
- simple backache
- strains
- bruises
- sprains

Warnings

For external use only

Allergy alert: If prone to allergic reaction from aspirin or salicylates, consult a doctor before use.

Do not use

- on wounds or damaged skin
- with a heating pad
- if you are allergic to any ingredients of this product

Stop use and ask a doctor if

- rash, itching or excessive skin irritation develops
- conditions worsen
- smptoms persist for more than 7 days
- symptoms clear up and occur again within a few days

PREGNANCY OR BREAST FEEDING

If pregnant or breast feeding, ask a health professional before use.

Keep out of reach of children. If swallowed, get medical help or contact a Poison Control Center right away.

Directions

adults and children 12 years of age and over:

- clean and dry affected area
- remove patch from film
- apply to affected area not more than 3 to 4 times daily
- remove patch from the skin after at most 8 hours' application

children under 12 years of age:

- consult a doctor

Other information

- avoid storing product in direct sunlight
- protect product from excessive moisture

Inactive ingredients

glyceryl hydrogenated rosinate, hydrated silica, mineral oil, polyethylene glycol 400, polyisobutylene (1300 MW), styrene/isoprene copolymer, YS resin, zinc oxide

DOSAGE AND ADMINISTRATION

Distributed by:

McKesson

One Post Street

San Franciso, CA 94104

www.healthmart.com/healthmartbrand